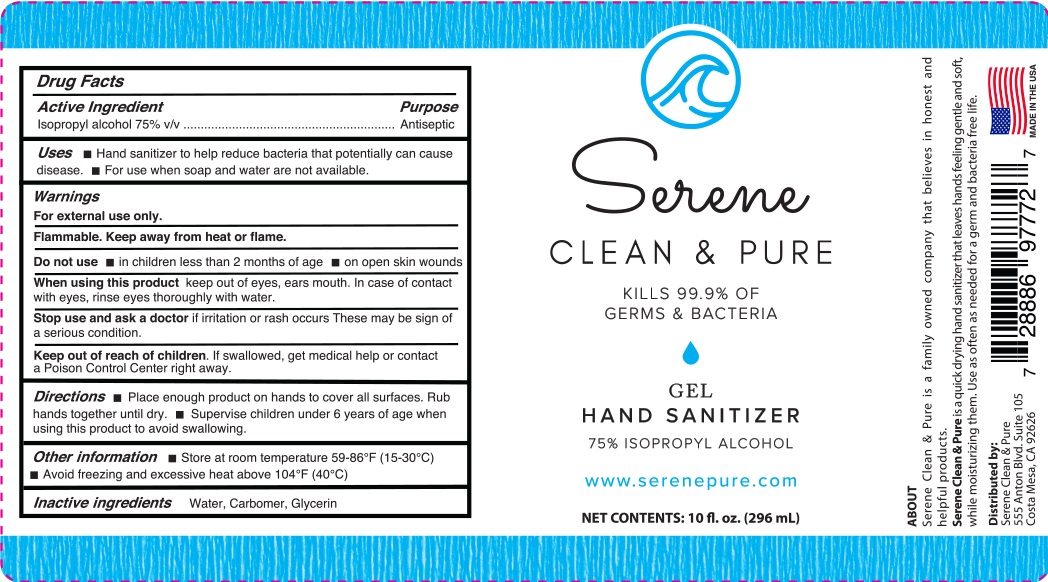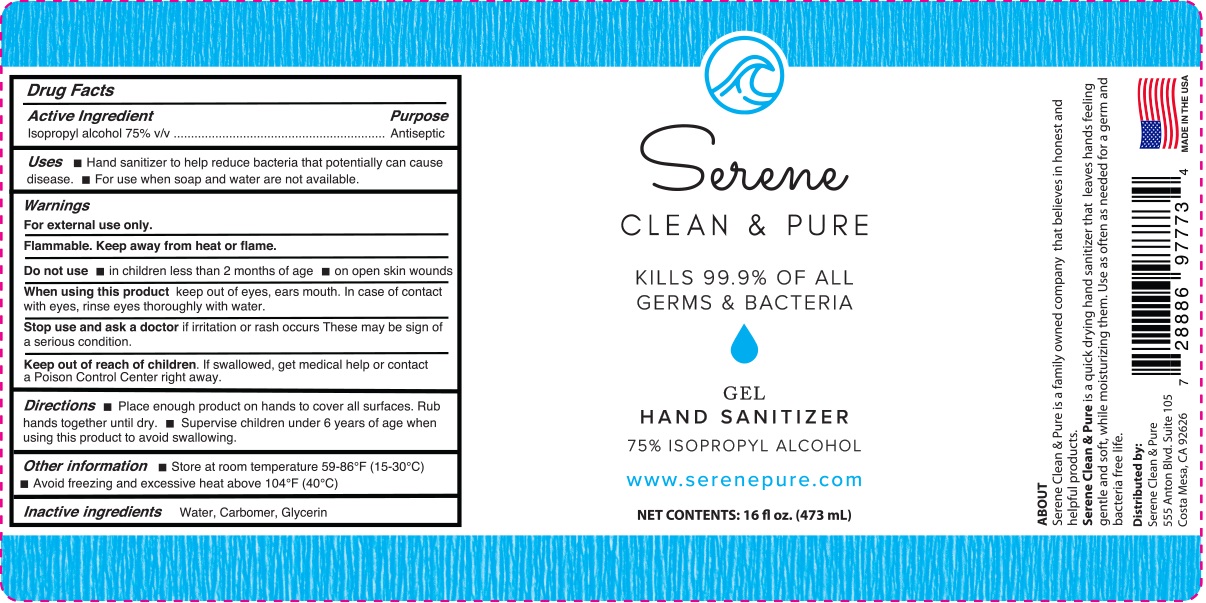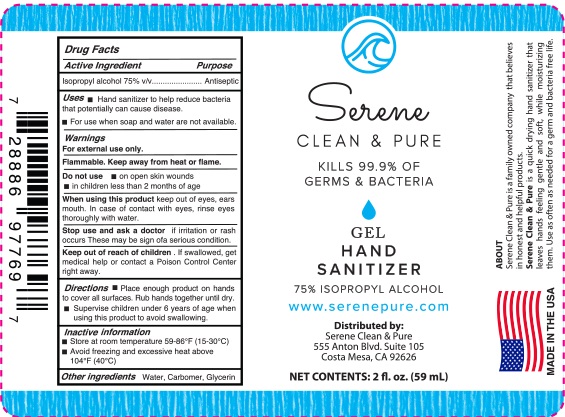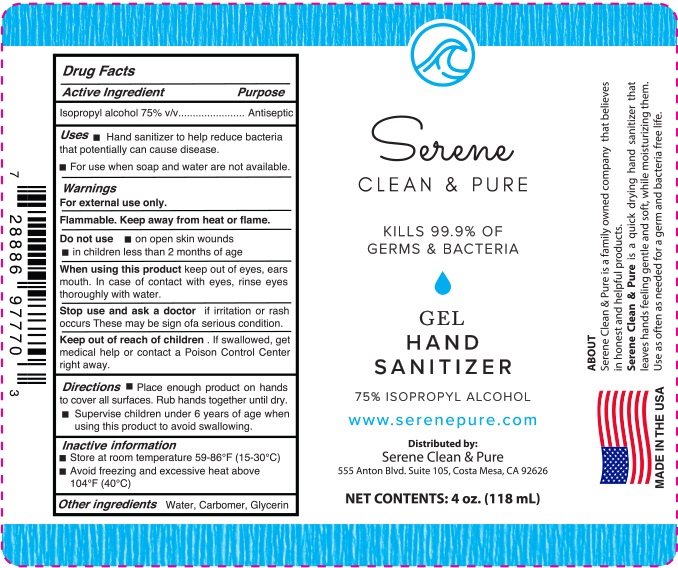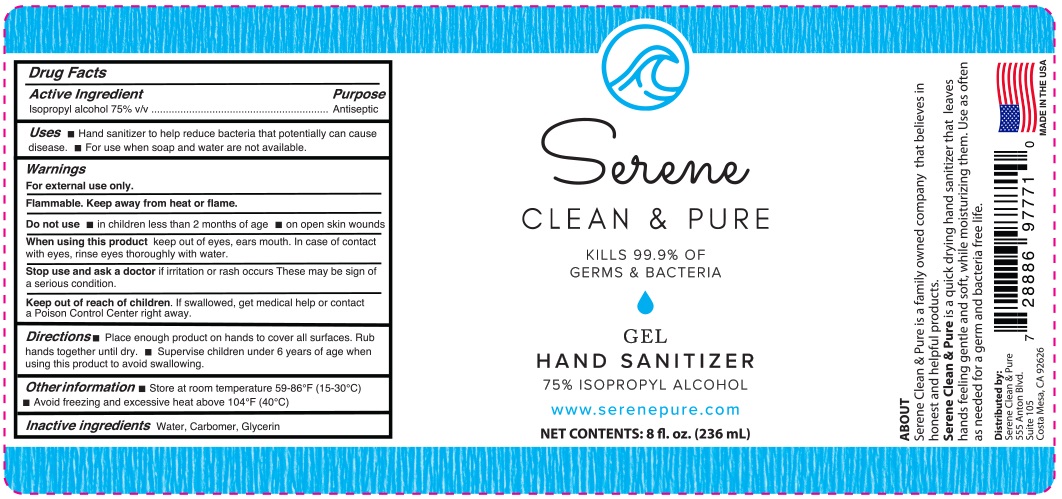 DRUG LABEL: Serene Clean and Pure Hand Sanitizer Gel
NDC: 78643-110 | Form: GEL
Manufacturer: Serene Clean & Pure LLC
Category: otc | Type: HUMAN OTC DRUG LABEL
Date: 20200716

ACTIVE INGREDIENTS: ISOPROPYL ALCOHOL 75 mL/100 mL
INACTIVE INGREDIENTS: GLYCERIN 1.45 mL/100 mL; WATER; CARBOMER HOMOPOLYMER, UNSPECIFIED TYPE

Serene Clean & Pure Gel Hand Sanitizer

Active ingredient

Isopropyl Alcohol 75% v/v. Purpose: Antiseptic

Purpose

Antiseptic

Use

Hand Sanitizer to help reduce bacteria that potentially can cause disease. For use when soap and water are not available.

Warnings

For external use only. Flammable. Keep away from heat or flame

Do not use

- in children less than 2 months of age
- on open skin wounds

When using this product

keep out of eyes, ears, and mouth. In case of contact with eyes, rinse eyes thoroughly with water.

Stop use and ask a doctor

if irritation or rash occurs. These may be signs of a serious condition.

Keep out of reach of children.

If swallowed, get medical help or contact a Poison Control Center right away.

Directions

- Place enough product on hands to cover all surfaces. Rub hands together until dry.
- Supervise children under 6 years of age when using this product to avoid swallowing.

Other information

- Store between 15-30C (59-86F)
- Avoid freezing and excessive heat above 40C (104F)

Inactive ingredients

Water, carbomer, glycerin

Package Label - Principal Display Panel

Serene Clean & Pure

Kills 99.9% of All Germs & Bacteria

Gel Hand Sanitizer

70% Isopropyl Alcohol

www.serenepure.com

ABOUT

Serene Clean & Pure is a family owned company that believes in honest and helpful products.

Serene Clean & Pure is a quickly drying hand sanitizer that leaves hands feeling gentle and soft, while moisturizing them. Use as often as needed for a germ and bacteria free life

Distributed by:

Serene Clean & Pure

555 Anton Blvd. Suite 105

Costa Mesa, CA 92626

2 fl. oz.

4 fl. oz.

8 fl. oz.

10 fl. oz.

16 fl. oz.